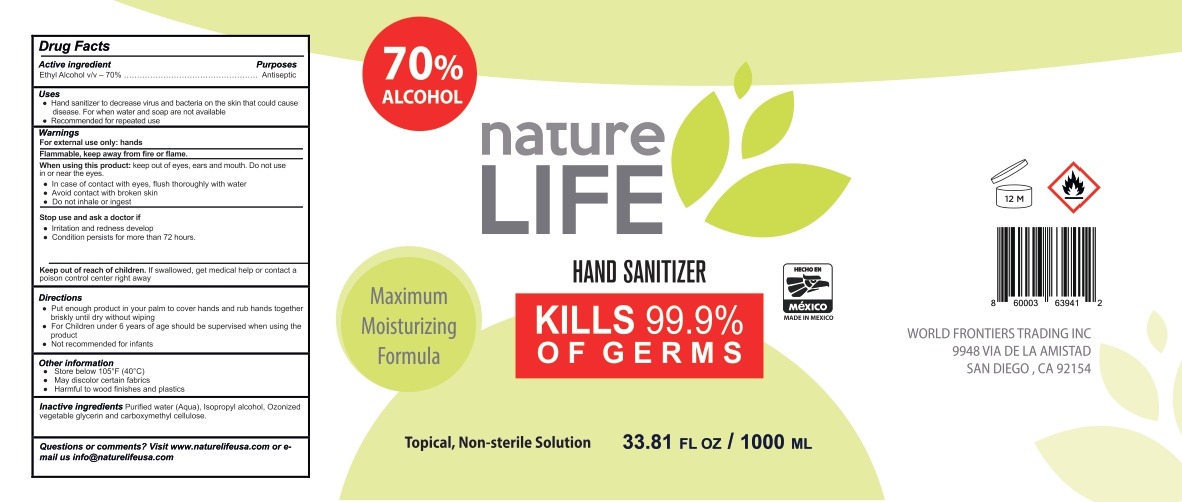 DRUG LABEL: HAND SANITIZER
NDC: 77210-0003 | Form: GEL
Manufacturer: EXPORTADORA IN & OUT S DE RL DE CV
Category: otc | Type: HUMAN OTC DRUG LABEL
Date: 20200517

ACTIVE INGREDIENTS: ALCOHOL 70 mL/100 mL
INACTIVE INGREDIENTS: ISOPROPYL ALCOHOL 5 mL/100 mL; WATER; GLYCERIN 3.17 mL/100 mL; CARBOXYMETHYLCELLULOSE 5 mL/100 mL

Active Ingredient

Ethyl Alchol v/v - 70%

Purposes

Antiseptic

Uses

Hand sanitizer to derease virus and bacteria on the skin that could cause disease. For when water and soap are not available

Recommended for repeated use

Warnings

For external use only: hands

Flammable, keep away from fire or flame

When using this product

keep out eyes, ears and mouth. Do not use in or near the eyes.

In case of contact with eyes, flush thorougly with water

Avoid contact with broken skin

Do not inhale or ingest

When using this product

Keep out of eyes, ears and mouth. Do not use in or near the eyes.

In case of contact eyes, flush thorougly with water

Avoid contact with broken skin

Do not inhale or ingest

Stop use and ask a doctor if

Irritation and redness develop

Conditions persists for more than 72 hours

Keep out of reach of children

If swallowed, get medical help or contact a posion control center right away

Other information

Sotre below 105 F (40C)

May discolor certain fabrics

Harmful to wood finishes and plastics

Inactive ingredients

Purified water (Aqua), Isopropyl alcohol, Ozonized vegetable glycerin and carboxymethul cellulose

PACKAGE LABEL

70% alcohol

Maximun moisturizing formula

Hand sanitizer

kills 99.9% of germs

topical, non steril solution

33.81fl oz/ 1000 ml